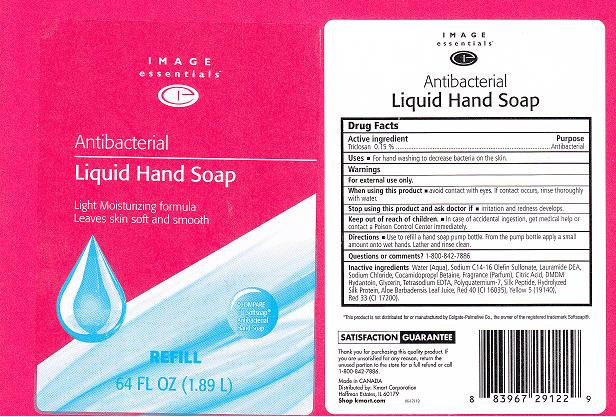 DRUG LABEL: ANTIBACTERIAL 
NDC: 49738-216 | Form: LIQUID
Manufacturer: KMART CORPORATION
Category: otc | Type: HUMAN OTC DRUG LABEL
Date: 20110602

ACTIVE INGREDIENTS: TRICLOSAN 0.15 L/100 L
INACTIVE INGREDIENTS: WATER; SODIUM C14 OLEFIN SULFONATE; LAURIC DIETHANOLAMIDE; SODIUM CHLORIDE; COCAMIDOPROPYL BETAINE; CITRIC ACID MONOHYDRATE; DMDM HYDANTOIN; GLYCERIN; EDETATE SODIUM; POLYQUATERNIUM-7 (70/30 ACRYLAMIDE/DADMAC; 1600 KD); BOMBYX MORI FIBER; BOMBYX MORI FIBER; ALOE VERA LEAF; FD&C YELLOW NO. 5; D&C RED NO. 33; FD&C RED NO. 40

DRUG FACTS

ACTIVE INGREDIENT

TRICLOSAN 0.15%

PURPOSE

ANTIBACTERIAL

USES

FOR HAND WASHING TO DECREASE BACTERIA ON THE SKIN.

WARNINGS

FOR EXTERNAL USE ONLY.

WHEN USING THIS PRODUCT

AVOID CONTACT WITH EYES. IF CONTACT OCCURS, RINSE THOROUGHLY WITH WATER.

STOP USING THIS PRODUCT AND ASK DOCTOR IF

IRRITATION AND REDNESS DEVELOPS.

KEEP OUT OF REACH OF CHILDREN

IN CASE OF ACCIDENTAL INGESTION, GET MEDICAL HELP OR CONTACT A POISON CONTROL CENTER IMMEDIATELY.

DIRECTIONS

USE TO REFILL A HAND SOAP PUMP BOTTLE. FROM THE PUMP BOTTLE APPLY A SMALL AMOUNT ONTO WET HANDS. LATHER AND RINSE CLEAN.

QUESTIONS OR COMMENTS

1-866-842-7886

INACTIVE INGREDIENTS

WATER, SODIUM C14-16 OLEFIN SULFONATE, LAURAMIDE DEA, SODIUM CHLORIDE, COCAMIDOPROPYL BETAINE, FRAGRANCE, CITRIC ACID, DMDM HYDANTOIN, GLYCERIN, TETRASODIUM EDTA, POLYQUATERNIUM-7, SILK PEPTIDE, HYDROLYZED SILK PROTEIN, ALOE BARBADENSIS LEAF JUICE, RED 40 (CI 16035), YELLOW 5 (19140), RED 33 (CI 17200)